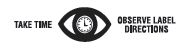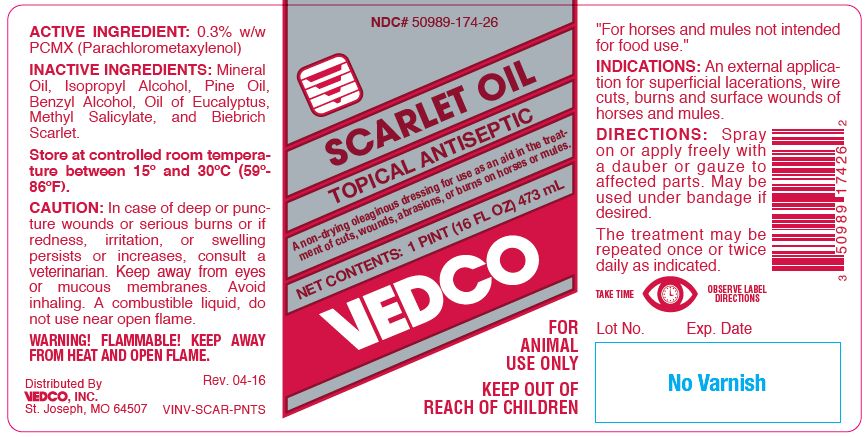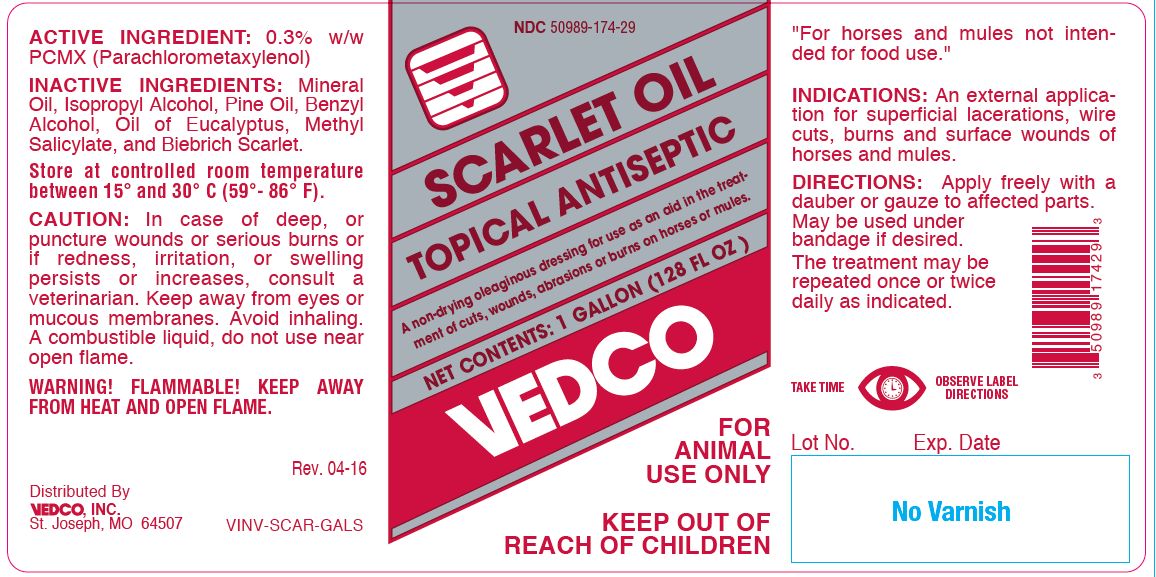 DRUG LABEL: Scarlet Oil
NDC: 50989-174 | Form: SOLUTION
Manufacturer: Vedco, Inc.
Category: animal | Type: OTC ANIMAL DRUG LABEL
Date: 20260223

ACTIVE INGREDIENTS: CHLOROXYLENOL 2.5 mg/1 mL

SCARLET OIL
TOPICAL ANTISEPTIC

PURPOSE

A non-drying oleaginous dressing for use as an aid in the treatment of cuts, wounds, abrasions or burns on horses or mules.

ACTIVE INGREDIENT:

0.3% w/w PCMX (Parachlorometaxylenol)

INACTIVE INGREDIENTS:

Mineral Oil, Isopropyl Alcohol, Pine Oil, Benzyl Alcohol, Oil of Eucalyptus, Methyl Salicylate, and Biebrich Scarlet.

STORAGE AND HANDLING

Store at controlled room temperature between 15° and 30° C (59°- 86° F).

CAUTION:

In case of deep, or puncture wounds or serious burns or if redness, irritation, or swelling persists or increases, consult a veterinarian. Keep away from eyes or mucous membranes. Avoid inhaling. A combustible liquid, do not use near open flame.

WARNING! FLAMMABLE! KEEP AWAY FROM HEAT AND OPEN FLAME.

FOOD SAFETY WARNING

"For horses and mules not intended for food use."

INDICATIONS:

An external application for superficial lacerations, wire cuts, burns and surface wounds of horses and mules.

DIRECTIONS:

Apply freely with a dauber or gauze to affected parts. May be used under bandage if desired.

The treatment may be repeated once or twice daily as indicated.

NET CONTENTS:

1 PINT (16 FL OZ) 473 mL VINV-SCAR-PNTS

1 GALLON (128 FL OZ) VINV-SCAR-GALS

INFORMATION FOR OWNERS/CAREGIVERS

Distributed By

VEDCO, INC.
St. Joseph, MO 64507